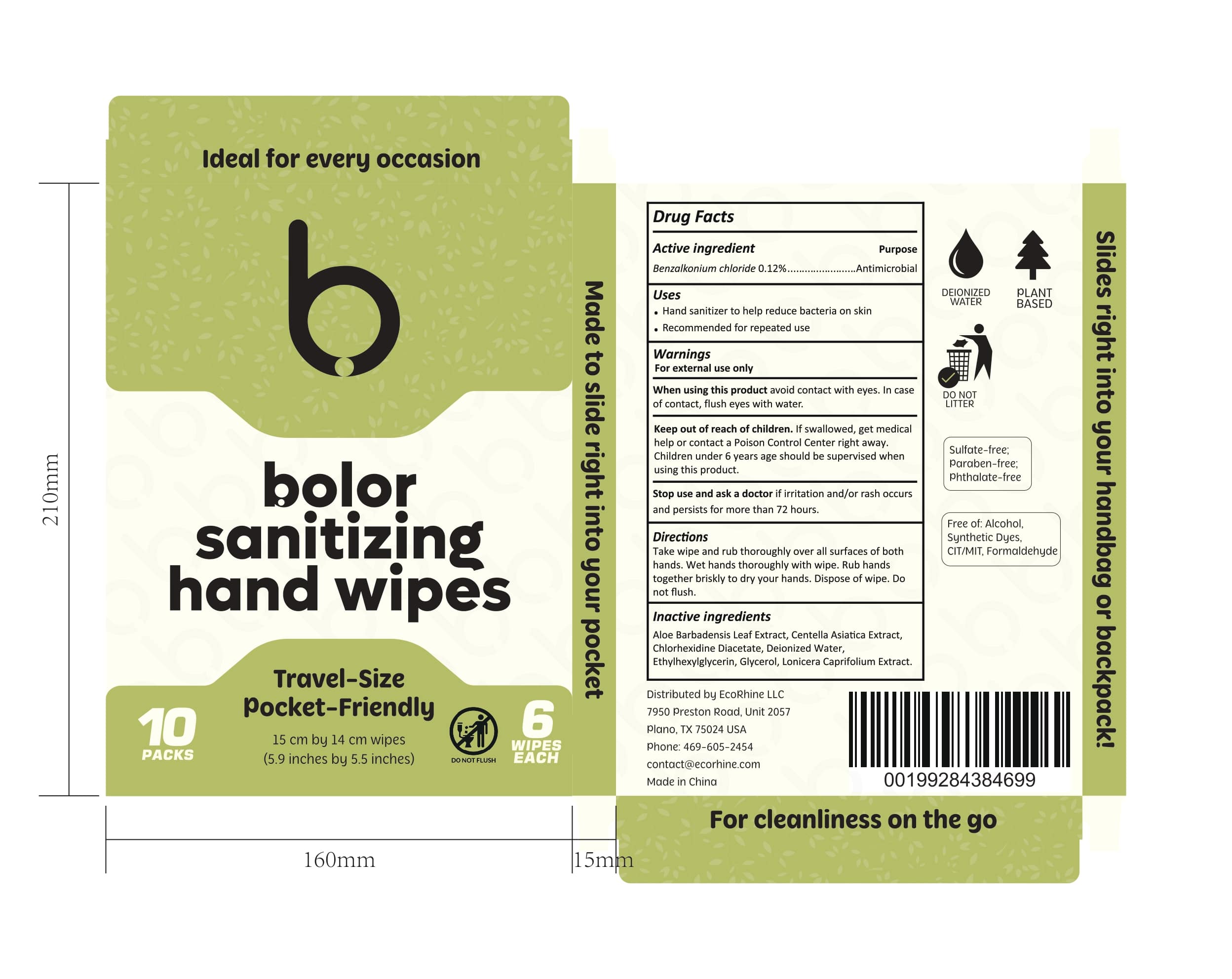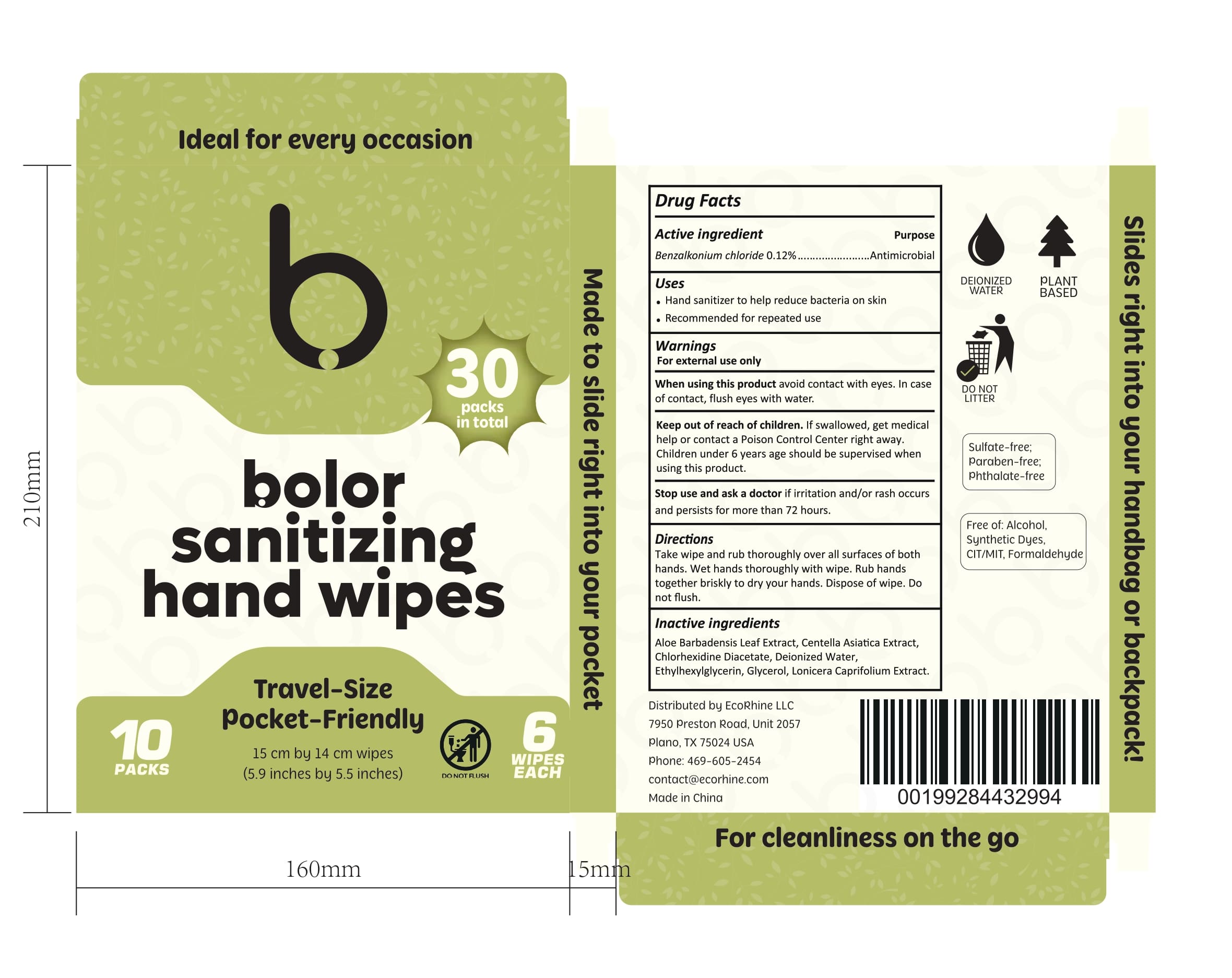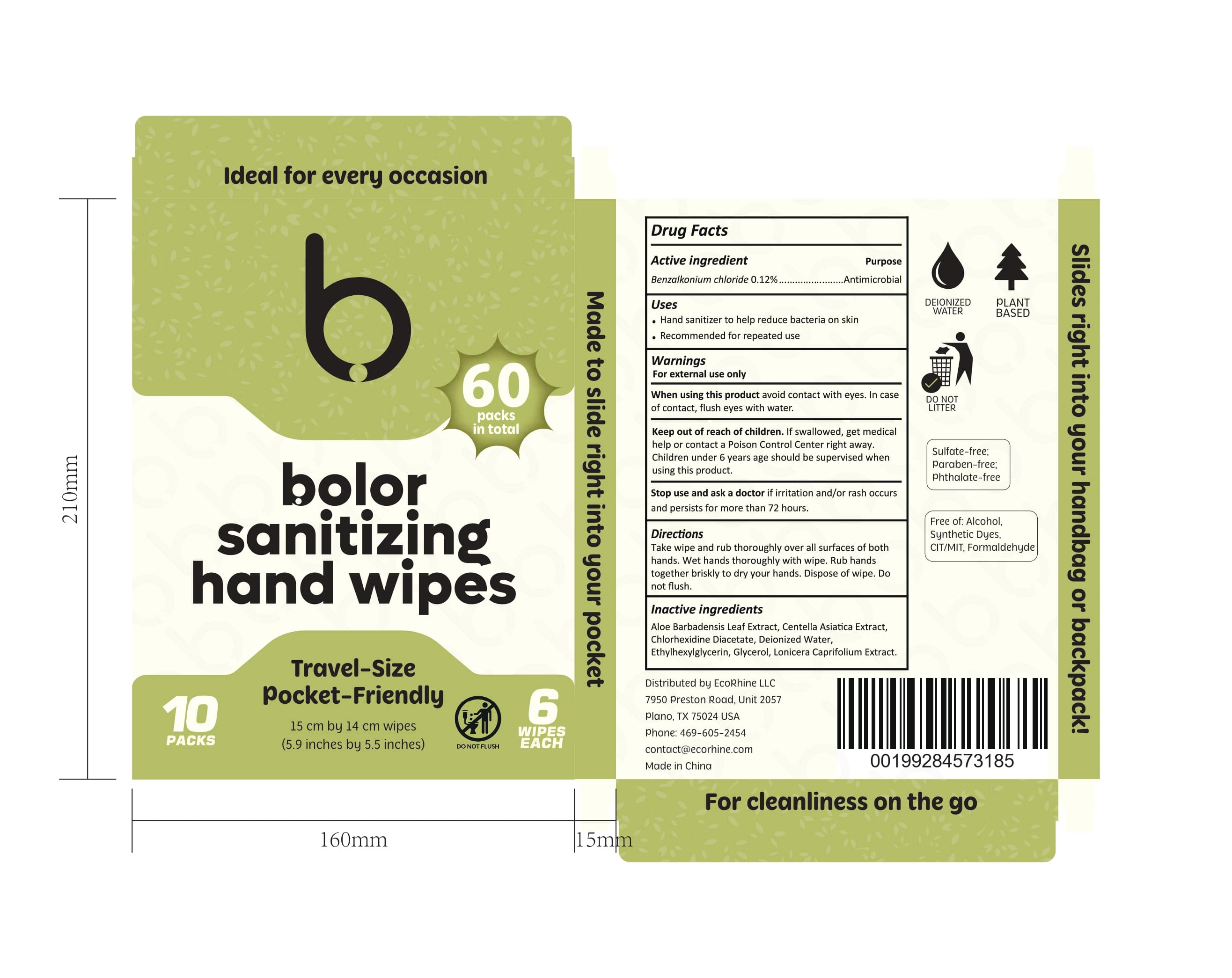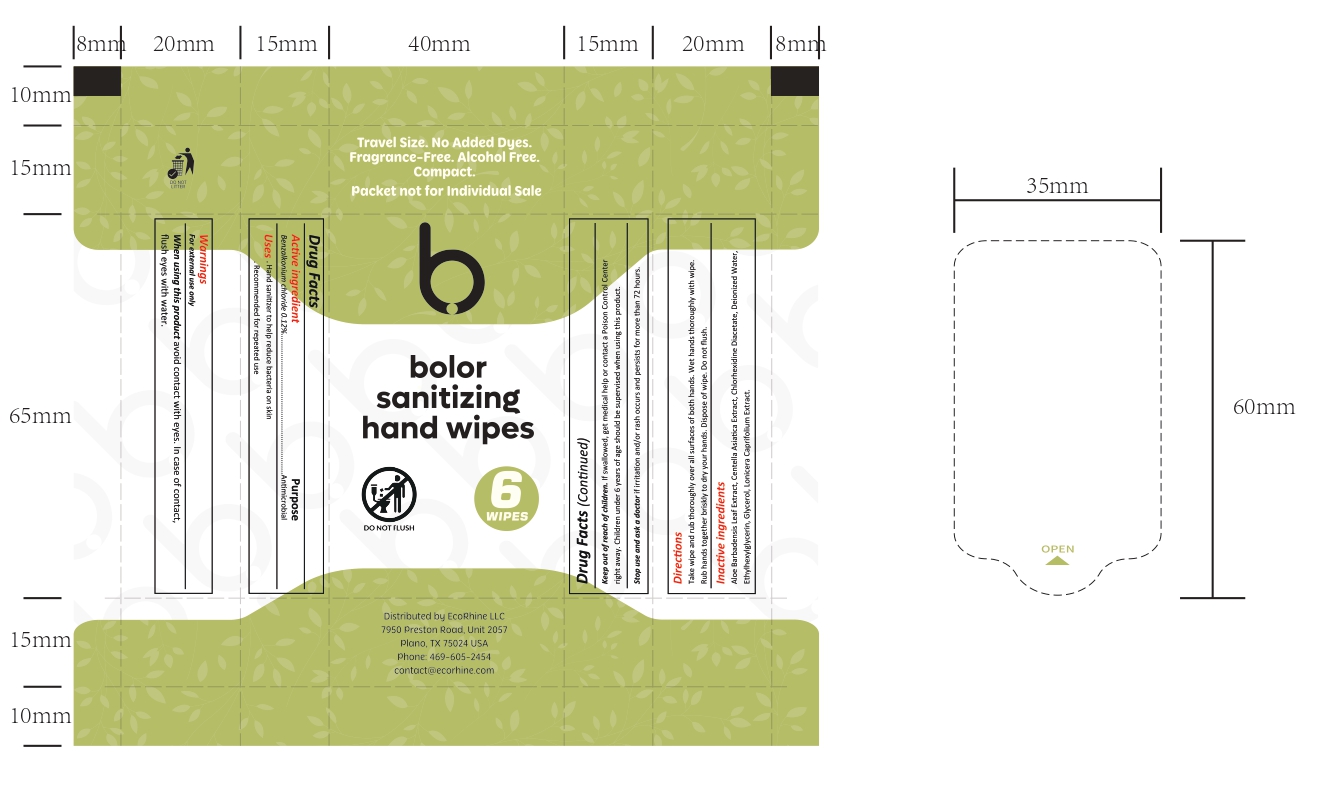 DRUG LABEL: bolor sanitizing hand wipes
NDC: 85577-002 | Form: SOLUTION
Manufacturer: EcoRhine LLC
Category: otc | Type: HUMAN OTC DRUG LABEL
Date: 20250629

ACTIVE INGREDIENTS: BENZALKONIUM CHLORIDE 0.12 mg/100 mg
INACTIVE INGREDIENTS: WATER; GLYCEROL FORMAL; ALOE BARBADENSIS LEAF JUICE; LONICERA CAPRIFOLIUM FLOWERING TOP; CENTELLA ASIATICA

Active ingredient Purpose

Benzalkonium chloride 0.12% Antimicrobial

Purpose

Antimicrobial

DOSAGE AND ADMINISTRATION

Directions Take wipe and rub thoroughly over all surfaces of both hands. Wet hands thoroughly with wipe. Rub hands together briskly to dry your hands. Dispose of wipe. Do not flush.

Warnings For external use only

INACTIVE INGREDIENT

Inactive ingredients Aloe Barbadensis Leaf Extract, Centella Asiatica Extract, Chlorhexidine Diacetate, Deionized Water, Ethylhexylglycerin, Glycerol, Lonicera Caprifolium Extract.

When using this product avoid contact with eyes. In case of contact, flush eyes with water

Keep out of reach of children. If swallowed, get medical help or contact a Poison Control Center right away. Children under 6 years age should be supervised when using this product.

PACKAGE LABEL

Drug Facts Active ingredient Purpose Benzalkonium chloride 0.12% Antimicrobial Uses Hand sanitizer to help reduce bacteria on skin Recommended for repeated use When using this product avoid contact with eyes. In case of contact, flush eyes with water. Keep out of reach of children. If swallowed, get medical help or contact a Poison Control Center right away. Children under 6 years age should be supervised when using this product. Stop use and ask a doctor if irritation and/or rash occurs and persists for more than 72 hours. Warnings For external use only Directions Take wipe and rub thoroughly over all surfaces of both hands. Wet hands thoroughly with wipe. Rub hands together briskly to dry your hands. Dispose of wipe. Do not flush. Inactive ingredients Aloe Barbadensis Leaf Extract, Centella AsiaƟca Extract, Chlorhexidine Diacetate, Deionized Water, Ethylhexylglycerin, Glycerol, Lonicera Caprifolium Extract.